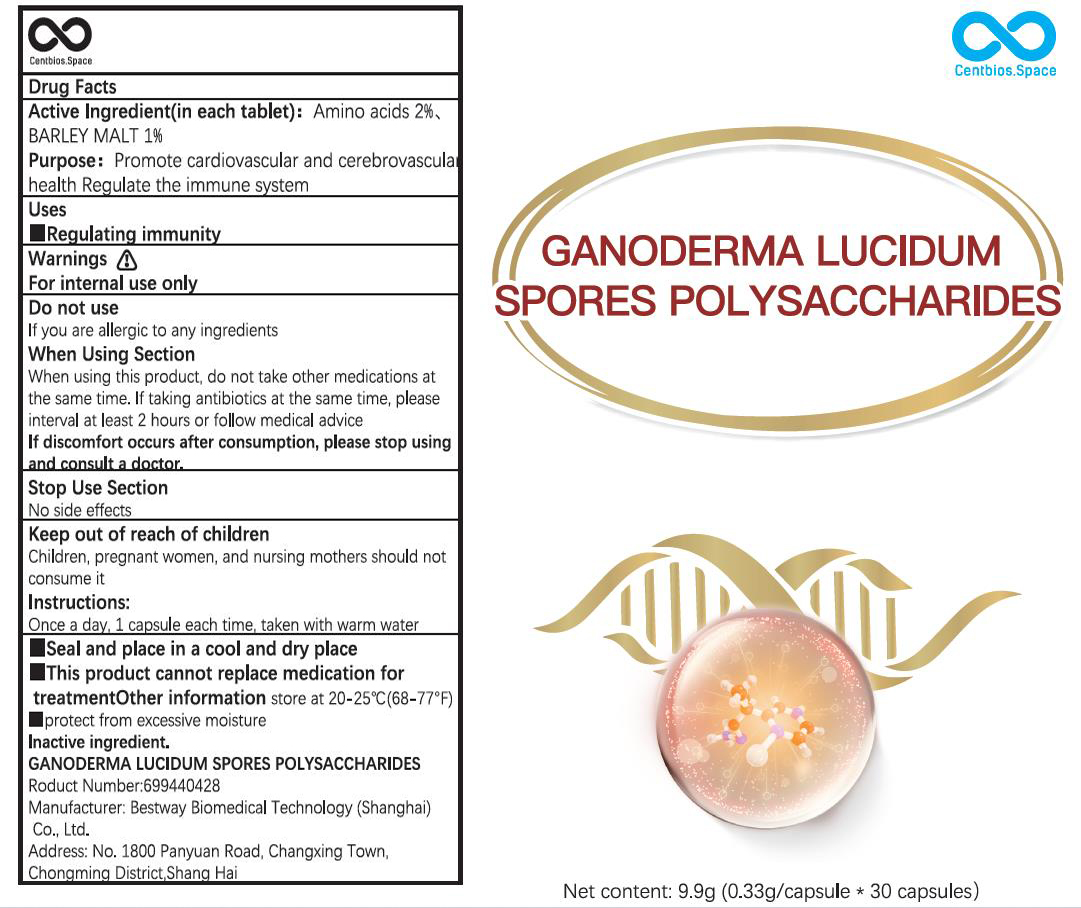 DRUG LABEL: GANODERMA LUCIDUM SPORES POLYSACCHARIDES
NDC: 83532-001 | Form: CAPSULE
Manufacturer: Bestway Biomedical Technology (Shanghai) Co., Ltd.
Category: otc | Type: HUMAN OTC DRUG LABEL
Date: 20230618

ACTIVE INGREDIENTS: AMINO ACIDS 2 g/9.9 1; BARLEY MALT 1 g/9.9 1
INACTIVE INGREDIENTS: REISHI

83532-001
GANODERMA LUCIDUM SPORES POLYSACCHARIDES

Active lngredient(in each tablet): Amino acids 2%, BARLEY MALT 1%

Purpose

Purpose: Promote cardiovascular and cerebrovascular health, Reaulate the immune system

Uses

Regulating immunity

Warnings

For internal use only

Do not use

lf you are allergic to any ingredients

When Using Section

When using this product, do not take other medications at the same time.
lf taking antibiotics at the same time, please interva at least 2 hours or follow medical advice.
lf discomfort occurs after consumption, please stop usingand consult a doctor.

Stop Use Section

No side effects

Keep out of reach of children

Children, pregnant women, and nursing mothers should not consume it

Instructions:

Once a day, 1 capsule each time, taken with warm water
Seal and place in a cool and dry place
This product cannot replace medication for treatment

Other information

store at 20-25°C(68-77°F)
protect from excessive moisture

lnactive ingredient.

GANODERMA LUCIDUM SPORES POLYSACCHARIDES

PACKAGE LABEL

83532-001-01
30 CAPSULE in 1BOX